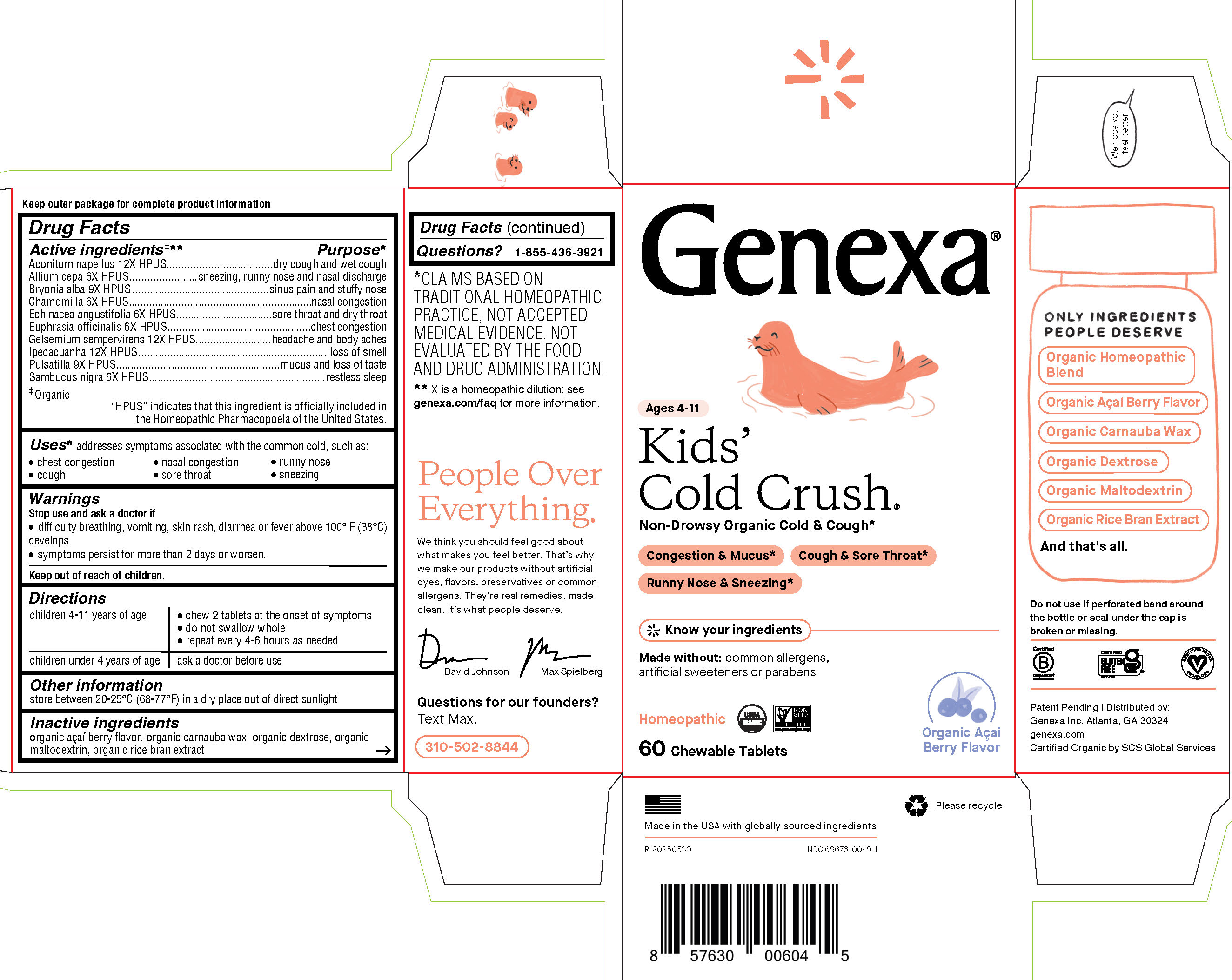 DRUG LABEL: Genexa Kids Cold Crush
NDC: 69676-0049 | Form: TABLET, CHEWABLE
Manufacturer: Genexa Inc.
Category: homeopathic | Type: HUMAN OTC DRUG LABEL
Date: 20251215

ACTIVE INGREDIENTS: ONION 6 [hp_X]/1 1; BRYONIA ALBA ROOT 9 [hp_X]/1 1; MATRICARIA CHAMOMILLA WHOLE 6 [hp_X]/1 1; ECHINACEA ANGUSTIFOLIA 6 [hp_X]/1 1; EUPHRASIA STRICTA 6 [hp_X]/1 1; GELSEMIUM SEMPERVIRENS ROOT 12 [hp_X]/1 1; IPECAC 12 [hp_X]/1 1; PULSATILLA PRATENSIS 9 [hp_X]/1 1; SAMBUCUS NIGRA FLOWER 6 [hp_X]/1 1; ACONITUM NAPELLUS 12 [hp_X]/1 1
INACTIVE INGREDIENTS: CARNAUBA WAX; MALTODEXTRIN; RICE BRAN; DEXTROSE; ACAI

Kids' Cold Crush

Drug Facts

Active ingredients‡**

Aconitum napellus 12X HPUS

Allium cepa 6X HPUS

Bryonia alba 9X HPUS

Chamomilla 6X HPUS

Echinacea angustifolia 6X HPUS

Euphrasia officinalis 6X HPUS

Gelsemium sempervirens 12X HPUS

Ipecacuanha 12X HPUS

Pulsatilla 9X HPUS

Sambucus nigra 6X HPUS

‡ Organic

"HPUS" indicates that this ingredient is officially included in the Homeopathic Pharmacopoeia of the United States.

Purpose*

dry cough and wet cough

sneezing, runny nose and nasal discharge

sinus pain and stuffy nose

nasal congestion

sore throat and dry throat

chest congestion

headache and body aches

loss of smell

mucus and loss of taste

restless sleep

Uses*

addresses symptoms associated with the common cold, such as:

- chest congestion
- nasal congestion
- runny nose
- cough
- sore throat
- sneezing

Warnings

Stop use and ask a doctor if

- difficulty breathing, vomiting, skin rash, diarrhea or fever above 100°F (38°C) develops
- symptoms persist for more than 2 days or worsen.

Keep out of reach of children.

Directions

children 4-11 years of age | - chew 2 tablets at the onset of symptoms - do not swallow whole - repeat every 4-6 hours as needed
children under 4 years of age | ask a doctor before use

Other information

store between 20-25°C (68-77°F) in a dry place out of direct sunlight

Inactive ingredients

organic açaÍ berry flavor, organic carnauba wax, organic dextrose, organic maltodextrin, organic rice bran extract

Questions?

1-855-436-3921

* CLAIMS BASED ON TRADITIONAL HOMEOPATHIC PRACTICE, NOT ACCEPTED MEDICAL EVIDENCE. NOT EVALUATED BY THE FOOD AND DRUG ADMINISTRATION.
** X is a homeopathic dilution; see genexa.com/faq for more information.

Do not use if perforated band around the bottle or seal under the cap is broken or missing.

Patent Pending | Distributed by:

Genexa Inc. Atlanta, GA 30324

genexa.com

Certified Organic by SCS Global Services

Made in the USA with globally sourced ingredients

NDC 69676-0049-1

PACKAGE LABEL

Genexa®
Ages 4-11
Kids' Cold Crush®

Non-Drowsy Organic Cold & Cough*
Congestion & Mucus*
Cough & Sore Throat*
Runny Nose & Sneezing*
Know your ingredients
Made without: common allergens, artificial sweeteners or parabens
Homeopathic
60 Chewable Tablets

Organic AçaÍ Berry Flavor